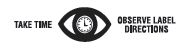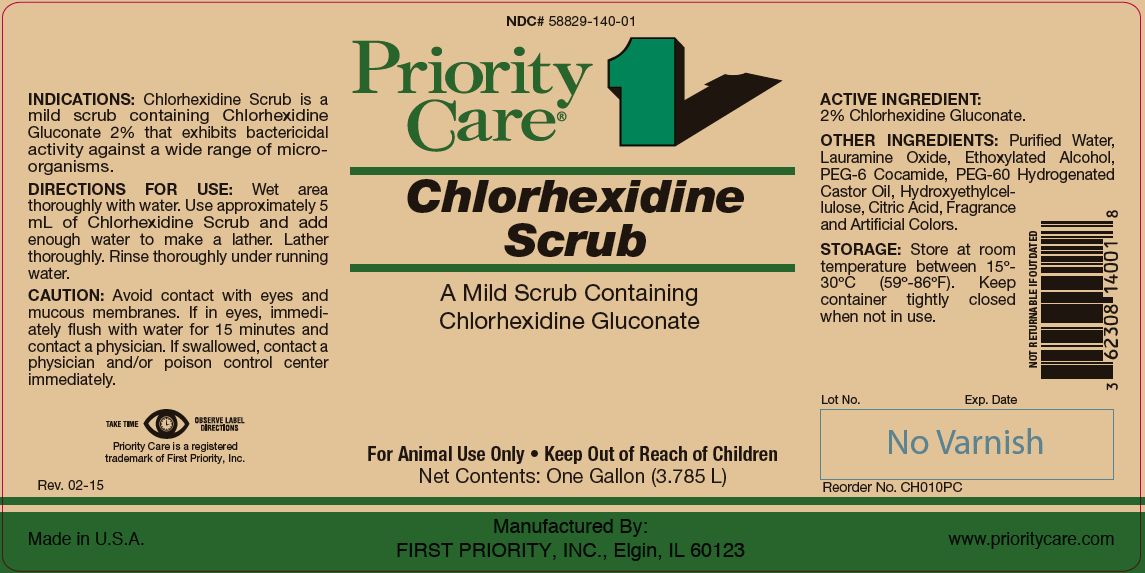 DRUG LABEL: CHLORHEXIDINE SCRUB
NDC: 58829-140 | Form: LIQUID
Manufacturer: FIRST PRIORITY INCORPORATED
Category: animal | Type: OTC ANIMAL DRUG LABEL
Date: 20221110

ACTIVE INGREDIENTS: CHLORHEXIDINE GLUCONATE 100.9 g/1 L

Chlorhexidine Scrub

INFORMATION FOR OWNERS/CAREGIVERS

A Mild Scrub Containing Chlorhexidine Gluconate

KEEP OUT OF REACH OF CHILDREN

For Animal Use Only • Keep Out of Reach of Children

INDICATIONS:

Chlorhexidine Scrub is a mild scrub containing Chlorhexidine Gluconate 2% that exhibits bactericidal activity against a wide range of microorganisms.

DIRECTIONS FOR USE:

Wet area thoroughly with water. Use approximately 5 mL of Chlorhexidine Scrub and add enough water to make a lather. Lather thoroughly. Rinse thoroughly under running water.

CAUTION:

Avoid contact with eyes and mucous membranes. If in eyes, immediately flush with water for 15 minutes and contact a physician. If swallowed, contact a physician and/or poison control center immediately.

ACTIVE INGREDIENT:

2% Chlorhexidine Gluconate.

OTHER INGREDIENTS:

Purified Water, Lauramine Oxide, Ethoxylated Alcohol, PEG-6 Cocamide, PEG-60 Hydrogenated Castor Oil, Hydroxyethylcellulose, Citric Acid, Fragrance and Artificial Colors.

STORAGE:

Store at room temperature between 15º-30ºC (59º-86ºF). Keep container tightly closed when not in use.

Net Contents:

One Gallon (3.785 L) Reorder No. CH010PC

INFORMATION FOR OWNERS/CAREGIVERS

Priority Care is a registered trademark of First Priority, Inc.

Manufactured By: FIRST PRIORITY, INC., Elgin, IL 60123

www.prioritycare.com

Made in U.S.A.